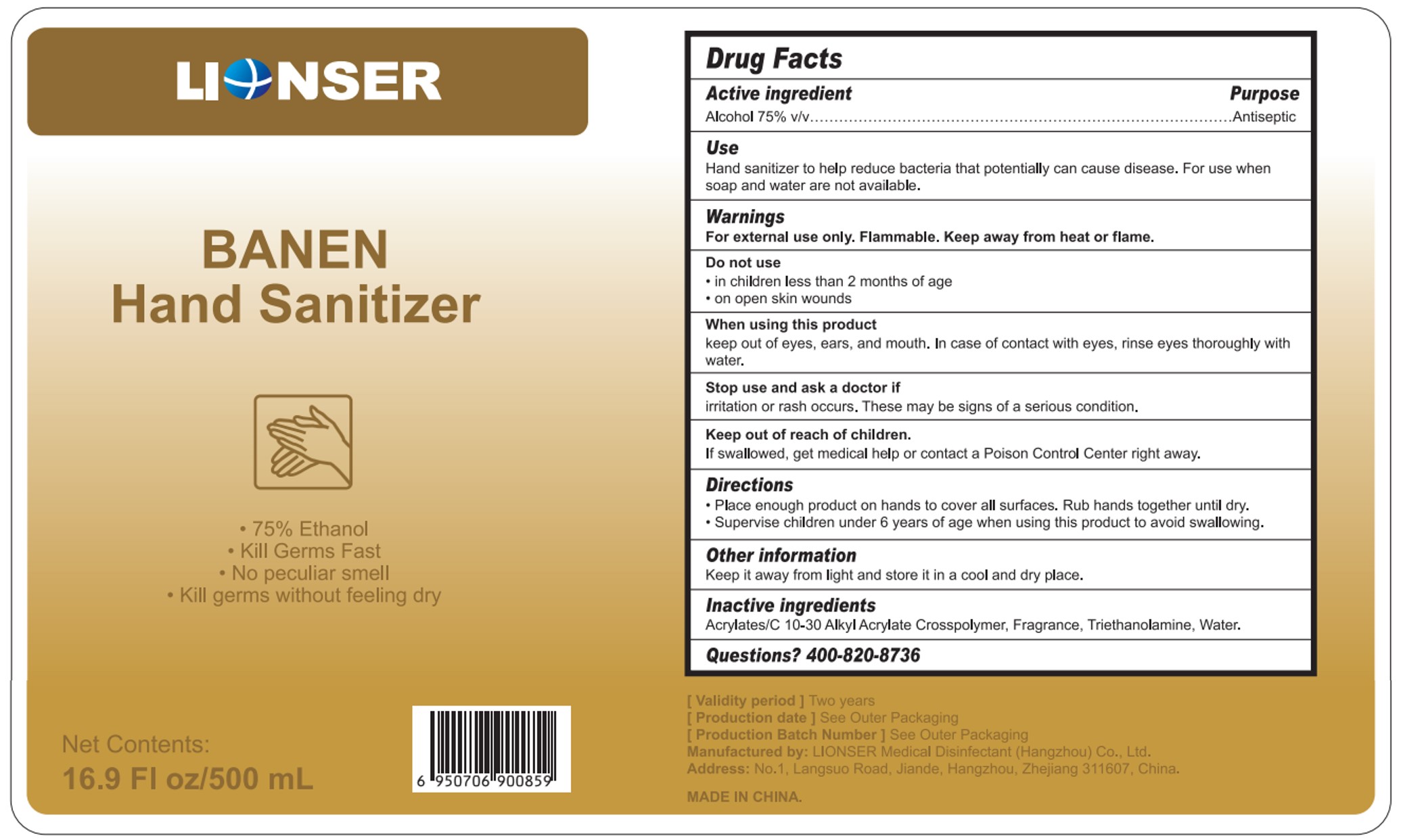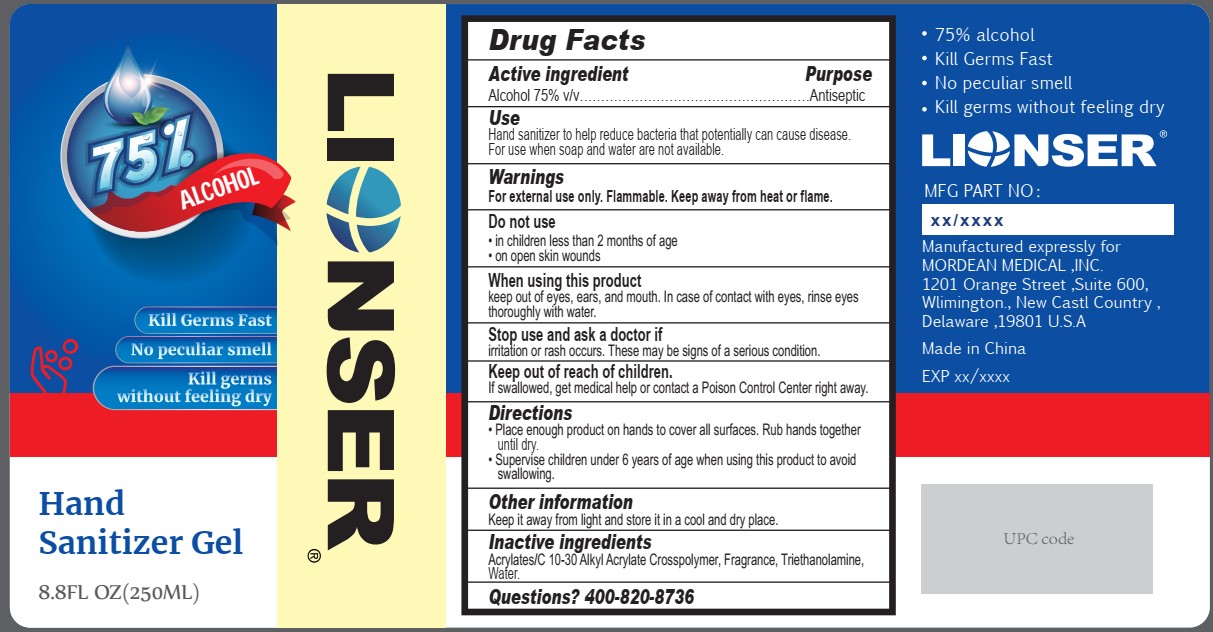 DRUG LABEL: Hand Sanitizer Gel
NDC: 52874-007 | Form: GEL
Manufacturer: LIONSER Medical Disinfectant(Hangzhou) Co., Ltd.
Category: otc | Type: HUMAN OTC DRUG LABEL
Date: 20211219

ACTIVE INGREDIENTS: ALCOHOL 75 mL/100 mL
INACTIVE INGREDIENTS: CARBOMER INTERPOLYMER TYPE B (ALLYL PENTAERYTHRITOL CROSSLINKED); TROLAMINE; FRAGRANCE LAVENDER & CHIA F-153480; WATER

Active Ingredient(s)

Alcohol 75% v/v. Purpose: Antiseptic

Purpose

Antiseptic, Hand Sanitizer

Use

Hand Sanitizer to help reduce bacteria that potentially can cause disease. For use when soap and water are not available.

Warnings

For external use only. Flammable. Keep away from heat or flame

Do not use

- in children less than 2 months of age
- on open skin wounds

When using this product keep out of eyes, ears, and mouth. In case of contact with eyes, rinse eyes thoroughly with water.
Stop use and ask a doctor if irritation or rash occurs. These may be signs of a serious condition.
Keep out of reach of children. If swallowed, get medical help or contact a Poison Control Center right away.

Stop use and ask a doctor if irritation or rash occurs. These may be signs of a serious condition.

Keep out of reach of children. If swallowed, get medical help or contact a Poison Control Center right away.

Directions

- Place enough product on hands to cover all surfaces. Rub hands together until dry.
- Supervise children under 6 years of age when using this product to avoid swallowing.

Other information

Keep it away from light and store it in a cool and dry place.

Inactive ingredients

Acrylates/C 10-30 Alkyl Acrylate Crosspolymer, Fragrance, Triethanolamine, Water.

Package Label - Principal Display Panel

250 mL NDC: 52874-007-01

Package Label - Principal Display Panel

500 mL NDC: 52874-007-02